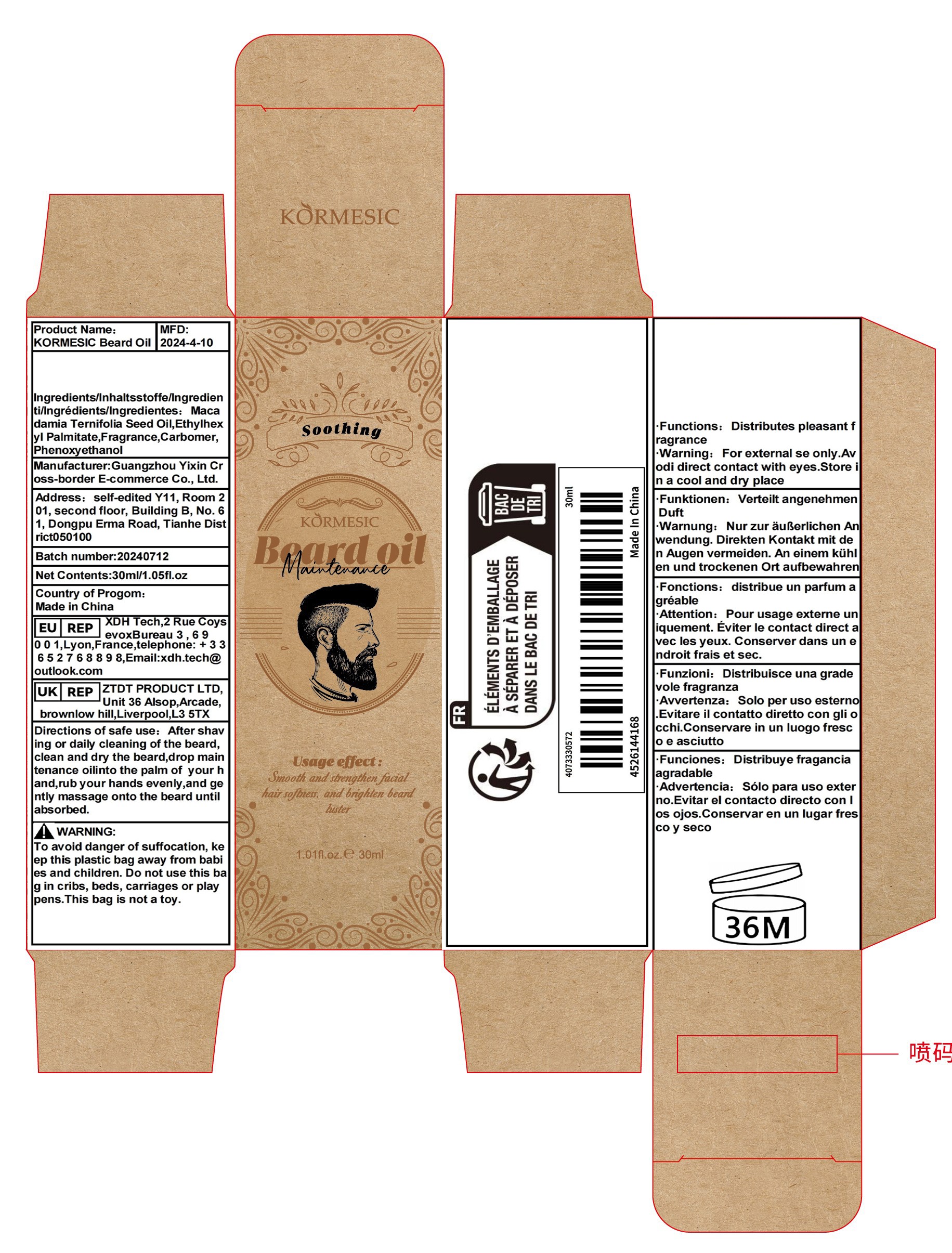 DRUG LABEL: KORMEsIC Beard Oil
NDC: 84778-014 | Form: LOTION
Manufacturer: Guangzhou Yixin Cross-border E-commerce Co., Ltd.
Category: otc | Type: HUMAN OTC DRUG LABEL
Date: 20241021

ACTIVE INGREDIENTS: MACADAMIA INTEGRIFOLIA SEED OIL 5 g/30 mL
INACTIVE INGREDIENTS: CARBOMER; ETHYLHEXYL PALMITATE; PHENOXYETHANOL; FRAGRANCE 13576

Active ingredients

Macadamia Ternifolia Seed Oil 5%
Rich in essential fatty acids and antioxidants, it helps moisturize the skin and maintain its elasticity.

Purpose

Softens and enhances facial hair, brightens beard.

Uses

Softens and enhances facial hair, brightens beard.After shaving or daily beard cleaning, drop the maintenance oil into the palm of your hand and rub your hands until absorbed.

Warnings

Due to different skin types, if you feel sensitive or uncomfortable after use, please stop using. Keep out of reach of children and do not swallow..

Dosage and administration

For external use only.

Do not use

Due to different skin types, if you feel sensitive or uncomfortable after use, please stop using. Keep out of reach of children and do not swallow.

When using section

Softens and enhances facial hair, brightens beard.After shaving or daily beard cleaning, drop the maintenance oil into the palm of your hand and rub your hands until absorbed.

stop use

Due to different skin types, if you feel sensitive or uncomfortable after use, please stop using. Keep out of reach of children and do not swallow.

Keep out of reach of children.lf swallowed, get medical help or contacta Poison Control Center right away.

Inactive ingredients

Ethylhexyl Palmitate,Fragrance,Carbomer,Phenoxyethanol